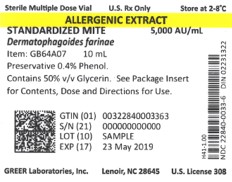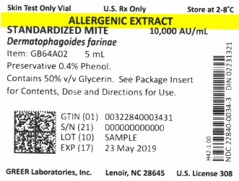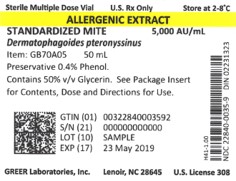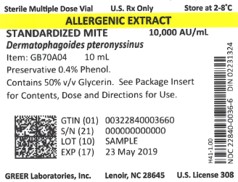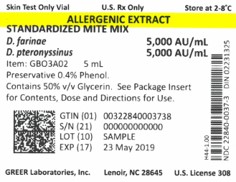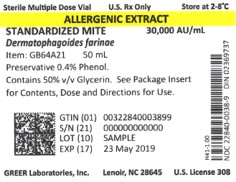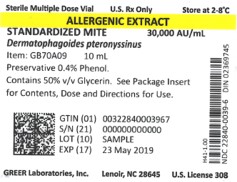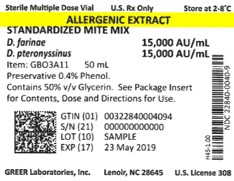 DRUG LABEL: Standardized Mite Dermatophagoides pteronyssinus
NDC: 22840-0039 | Form: CONCENTRATE
Manufacturer: Greer Laboratories, Inc.
Category: prescription | Type: HUMAN PRESCRIPTION DRUG LABEL
Date: 20250206

ACTIVE INGREDIENTS: DERMATOPHAGOIDES PTERONYSSINUS 30000 [AU]/1 mL
INACTIVE INGREDIENTS: SODIUM CHLORIDE; GLYCERIN; SODIUM BICARBONATE; PHENOL

HIGHLIGHTS OF PRESCRIBING INFORMATION

These highlights do not include all the information needed to use Greer Standardized Mite Extracts safely and effectively. See full prescribing information for Greer Standardized Mite Extracts.
Standardized Mite Extract (Dermatophagoides farinae)
Standardized Mite Extract (Dermatophagoides pteronyssinus)
Standardized Mite Extract Mixture (Dermatophagoides farinae and Dermatophagoides pteronyssinus)
Solution for percutaneous, intradermal, or subcutaneous administration
Initial U.S. Approval: 1987

WARNING: ANAPHYLAXIS

See full prescribing information for complete boxed warning.

- Do not inject intravenously (2.2)
- Allergenic extracts may cause severe life-threatening systemic reactions, including the rare occurrence of anaphylaxis or death (5.1)
- Intended for use only by experts experienced in administering allergic extracts and trained to provide emergency treatment (5.1)
- Initial dose must be based on skin test (2.1)
- Observe patients in the office for at least 30 minutes following treatment. Emergency measures andpersonnel trained in their use must be available immediately in the event of life threatening reaction (5.1)
- Immunotherapy may not be suitable for patients with medical conditions that reduce their ability tosurvive a systemic reaction (5)

1 INDICATIONS AND USAGE

Greer Standardized Mite Extracts are allergenic extracts indicated for:

- Diagnosis of skin test reactivity to dust mite allergen (1)
- Treatment of mite-induced allergic asthma, rhinitis and conjunctivitis in patients that show hypersensitivity to dust mites based on clinical history, allergen exposure history, and skin test reactivity (1)

2 DOSAGE AND ADMINISTRATION

The extracts are diluted with sterile diluents for allergenic extracts when used for intradermal testing or subcutaneous immunotherapy. Dosages vary by mode of administration, and by individual response and tolerance.

- Administered percutaneouslly for diagnostic testing (2.1); stock concentrate 10,000 Allergy Units/mL (2.1)
- Administered intradermally for diagnostic testing (2.1); stock concentrate 5,000, 10,000, or 30,000 Allergy Units/mL (2.3)
- Administered subcutaneously for immunotherapy (2.2); stock concentrate of 5,000, 10,000,or 30, 000 Allergy Units/mL (2.3)

3 DOSAGE FORMS AND STRENGTHS

- For percutaneous testing, Greer Standardized Mite Extract stock concentrates containing 10,000 Allergy Units/mL of Dermatophagoides farinae (D. farinae), Dermatophagoides pteronyssinus (D. pteronyssinus), or both D. farinae and D. pteronyssinus are supplied in 5 mL dropper vials (3)
- For intradermal testing or immunotherapy, Greer Standardized Mite Extracts stock concentrates containing a total of 5,000, 10,000 or 30,000 Allergy Units/mL of D. farinae, D. pteronyssinus, or a mixture of D. farinae and D. pteronyssinus are supplied in 10, 30 and 50 mL multiple-dose vials (3)

4 CONTRAINDICATIONS

None (4)

5 WARNINGS AND PRECAUTIONS

All concentrates of Greer Standardized Mite Extracts can cause serious systemic reactions of varying degrees of severity, including anaphylactic shock and death, particularly in patients:

- With labile or steroid-dependent asthma (5.1)
- With extreme sensitivity to allergen(s) (5.1)
- Who are currently using beta blockers (5.2)
- Who are on an accelerated immunotherapy build-up schedule (5.1)
- Who are being changed from one allergenic extract to another (5.1)
- Who are receiving high doses of allergen extracts (5.1)

6 ADVERSE REACTIONS

- Systemic reactions may be fatal or near fatal (6)
- Systemic reactions (e.g. generalized skin erythema, urticaria, pruritus, angioedema, rhinitis, wheezing, laryngeal edema, and hypotension) occur in 4-7% of patients
- The most common reactions are local reactions at the injection site (e.g., erythema, itching, swelling, tenderness, pain), occuring in 26% to 82% of patients (6)

To report SUSPECTED ADVERSE REACTIONS, contact Greer Laboratories, Inc., at 1-855-274-1322 or the FDA at 1-800-FDA-1088 or www.fda.gov/medwatch

7 DRUG INTERACTIONS

- Patients who are receiving beta agonists may be unresponsive to the usual doses of epinephrine used to treat serious systemic reactions, including anaphylaxis (7.1)
- Patients should discontinue medications known to suppress the histamine response prior to skin testing including: antihistamines (7.2), tricyclics (7.4), and topical corticosteroids and topical anesthetics (7.3)

8 USE IN SPECIFIC POPULATIONS

- Pregnancy: No human or animal data. Use only if clearly needed (8.1)
- Autoimmune Disease: Immunotherapy may exacerbate the autoimmune disease. Use only if clearly needed (5.3)

See 17 for PATIENT COUNSELING INFORMATION.

Revised: 1/2013

FULL PRESCRIBING INFORMATION

WARNING: ANAPHYLAXIS

- Do not inject intravenously. (2.2)
- Allergenic extracts may potentially elicit a severe life-threatening systemic reaction, rarely resulting in death. (5.1)
- This allergenic product is intended for use only by physicians who are experienced in the administration of allergenic extracts and the emergency care of anaphylaxis, or for use under the guidance of an allergy specialist. (5.1)
- The initial dose must be based on skin test. (2.1)
- Observe patients in the office for at least 30 minutes following treatment. Emergency measures and personnel trained in their use must be available immediately in the event of life threatening reaction. (5.1)
- Immunotherapy may not be suitable for patients with medical conditions that reduce their ability to survive a systemic reaction, including significant cardiovascular and/or pulmonary diseases. Patients who are receiving beta blockers may be unresponsive to the usual doses of epinephrine used to treat systemic reactions, including anaphylaxis. (5.2)

1 INDICATIONS AND USAGE

Greer Standardized Mite (Dermatophagoides farinae and/or Dermatophagoides pteronyssinus) Extracts are allergenic extracts indicated for:

- skin test diagnosis of mite allergy
- treatment of patients with mite-induced allergic asthma, rhinitis and conjunctivitis.

For immunotherapy, patients must show hypersensitivity to Dermatophagoides farinae (D. farinae) or Dermatophagoides pteronyssinus (D. pteronyssinus) based on their clinical history, allergen exposure history, and skin test reactivity.

2 DOSAGE AND ADMINISTRATION

Do not inject intravenously.

Greer Standardized Mite extracts are diluted with sterile diluent for allergenic extracts when used for intradermal testing or subcutaneous immunotherapy. Dosages vary by mode of administration, and by individual response and tolerance. Parenteral drug products should be inspected visually for particulate matter and discoloration prior to administration, whenever solution and container permit. Greer Standardized Mite Extracts should be a light brown solution that is free of particulate matter. If particulate matter is observed then the solution should be discarded.

2.1 Diagnostic Testing

For diagnosis of a patient with a suspected allergy to either species of dust mite (D. farinae or D. pteronyssinus), diagnostic skin testing should include the standardized mite mixture or the single-species mite extracts.

- If a skin test with the standardized mite mixture elicits a positive reaction, then the single-species mite extracts can be used to determine the degree of sensitivity to each, and to guide in the selection of extracts and their concentration for immunotherapy, if indicated.
- A positive skin test reaction to any allergen must be interpreted in light of the patient's history of symptoms, the time of year, and known exposure to environmental allergens.

2.1.1 Percutaneous Skin Testing

For percutaneous (scratch, prick, or puncture) testing, use 10,000 Allergy Units/mL Greer Standardized Mite Extract stock concentrate in dropper vials. If patient is suspected of having exquisite sensitivity, such as anaphylaxis, to certain foods and drugs, initiate percutaneous testing with several serial 10-fold dilutions of the usual test concentration.

- For scratch tests, scarify the skin, and then apply one drop of the extract to the scratch.
- For prick tests, place one drop of extract on the skin and pierce through the drop into the skin with a slight lifting motion.
- For puncture tests, place one drop of extract on the skin and pierce through the drop perpendicular to the skin.

When using percutaneous test devices, follow the directions provided with the test devices.

Include a positive control to detect false negative responses to skin testing, which may occur if serum levels of antihistamines remain from prior medication administration [see Drug Interactions (7.2)]. A glycerinated histamine phosphate diluted to 10 mg/mL (6 mg/mL histamine base) may be used as the positive control.

Include a negative control to detect false positive responses, which can occur when the patient has a non-specific reaction to the diluent. A 50% glycerosaline solution may be used as the negative control.

Read skin tests 15-20 minutes after exposure. Record the induration (wheal) and erythema (flare) response by noting the longest diameter of each, or by the sum of the longest erythema diameter and the mid-point orthogonal diameters of erythema (ΣE).

Percutaneous testing devices often have their own grading systems, as these devices may cause different degrees of trauma to the skin and deliver different volumes of allergenic extract. Follow grading instructions for the device used.

2.1.2 Intradermal Skin Testing

Intradermal tests are commonly used when the reaction to percutaneous testing is negative or equivocal but the patient has a strong clinical history of symptoms triggered by exposure to a specific allergen. Because immediate systemic reactions are more common with intradermal testing, prescreening with percutaneous testing is a practical safety measure.^1

Dilute the stock concentrate with sterile diluent. Use saline with human serum albumin (HSA), buffered saline, or saline. If prescreening is not done, or if patients are expected to be high risk, precautions should be observed since some patients have experienced anaphylaxis and death.

- Patients who do not react to percutaneous skin testing should be tested intradermally at a starting dose of 0.02 to 0.05 mL of a 50 Allergy Units/mL extract dilution.
- Patients suspected of being highly allergic should first receive a test dose of 0.02 to 0.05 mL of a 0.05 Allergy Units/mL extract dilution.
- If the initial dose test is negative, subsequent intradermal tests using increasingly stronger doses may be performed up to the maximum recommended strength of 200 Allergy Units/mL.
- If percutaneous skin testing was not performed, include a positive control to detect false negative responses to skin testing, which may occur if serum levels of antihistamines remain from prior medication administration [see Drug Interactions (7.2)]. A glycerinated histamine phosphate diluted to 0.5 mg/mL (0.18 mg/mL histamine base) or aqueous histamine phosphate 0.275 mg/mL (0.1 mg/mL histamine base) may be used as the positive control.
- If percutaneous skin testing was not performed, include a negative control to detect false positive responses, which can occur when the patient has a non-specific reaction to the diluent. A 1% glycerin in 0.9% saline solution may be used as the negative control.
- Measure the wheal-and-flare response after 15-20 minutes, which may be graded using variou methods as described in the instructions for the device used.

The mean dose of Greer dust mite allergen required to elicit a positive intradermal test result (ΣE > 50 mm) in a total of 83 mite puncture test positive (ΣE > 20 mm) persons is shown in Table 1.

Table 1. Intradermal Reactivity to Mite Allergens
Allergen | Number of Persons | Dose to Elicit 50 mm Sum of Diameter Erythema Reaction
 |  | Mean (AU*/mL) | Range (AU/mL)
D. farinae | 46 | 0.00856 | 0.00004 - 1.75935
D. pteronyssinus | 37 | 0.00570 | 0.00002 - 1.36341**

* Allergy Units
** Data is available on file with Greer

2.2 Immunotherapy

Subcutaneous injection only.

Subcutaneous injections for immunotherapy should be prepared by dilution of stock concentrate based on patient's reactivity. Stock concentrations of Greer Standardized Mite Extract are available in 5,000 Allergy Units/mL, 10,000 Allergy Units/mL, 30,000 Allergy Units/ mL for immunotherapy. See Table 2 for dilution preparation. Also see Dosage Modification Guidelines 2.2.1).

- The initial dose of the extract should be based on the percutaneous test reactivity. In patients who appear to be exquisitely sensitive by history and skin test, the initial dose of the extract should be 0.1 mL of a 0.005 to 0.05 Allergy Units/mL dilution. Patients with lesser sensitivity may be started at a 0.5 to 5 Allergy Units/mL dilution.
- The dose of allergenic extract is increased at each injection by no more than 50% of the previous dose, and the next increment is governed by the response to the last injection.
- Large local reactions which persist for longer than 24 hours are generally considered an indication for repeating the previous dose or reducing the dose at the next administration.
- Any evidence of a systemic reaction is an indication for a significant reduction (at least 75%) in the subsequent dose. Repeated systemic reactions, even of a mild nature, are sufficient reason for the cessation of further attempts to increase the reaction-causing dose.
- Severe reactions require a decrease in the next dose by at least 50%. Proceed cautiously in subsequent dosing.
- A maximum tolerated maintenance dose should be selected based on the patient's clinical response and tolerance. Doses larger than 0.2 mL of the concentrate are rarely administered because an extract in 50% glycerin may cause discomfort upon injection.
- Since the two mite species tend to cross-react, consider the total Allergy Units content in determining the maximum maintenance dose of the mixture.

2.2.1 Dosage Modifications Guidelines for Immunotherapy

The following conditions may indicate a need to withold or reduce the dosage of immunotherapy. In situations prompting dose reduction, once the reduced dose is tolerated, a cautious increase in dosage can be attempted.

Immunotherapy should be withheld or reduced in dosage if the following concurrent conditions exist:

- Severe symptoms of rhinitis and/or asthma;
- Infection accompanied by fever; or
- Exposure to excessive amounts of clinically relevant allergen prior to a scheduled injection.

Changing to a different lot of extract: All extracts lose potency over time. A fresh extract may have an effective potency that is substantially greater than that of older extracts. Therefore, the first dose from the fresh vial should not exceed a 25% increase of the previous dose or a 75% reduction of the previous dose, assuming both extracts contain comparable amounts of allergen, defined by Allergy Units.

Unscheduled Gaps between Treatments: Patients may lose tolerance for allergen injections during prolonged periods between doses, thus increasing their risk for an adverse reaction. The duration of tolerance between injections varies from patient to patient.

- During the build-up phase, when patients receive injections 1 to 2 times per week, it is customary to repeat or even reduce the extract dosage if there has been a substantial time interval between injections. This depends on 1) the concentration of allergen immunotherapy extract that is to be administered, 2) a previous history of systemic reactions, and 3) the degree of variation from the prescribed interval of time, with longer intervals since the last injection leading to greater reductions in the dose to be administered. This suggested approach to dose modification due to unscheduled gaps between treatments during the build-up phase is not based on published evidence. The individual physician should use this or a similar protocol as a standard operating procedure for the specific clinical setting.
- Similarly, if large unscheduled gaps occur during maintenance therapy, it may be necessary to reduce the dosage. The individual physician should devise a protocol as a standard operating procedure for his or her specific clinical setting in determining how to modify doses of allergen immunotherapy due to unscheduled gaps in treatment.

The extract previously used is from another manufacturer: Since manufacturing processes and sources of raw materials differ among manufacturers, the interchangeability of extracts from different manufacturers cannot be assured. The starting dose of the extract from a different manufacturer should be greatly decreased even though the extract is the same formula and dilution. In general, a dose reduction of 50-75% of the previous dose should be adequate, but each situation must be evaluated separately considering the patient's history of sensitivity, tolerance of previous injections, and other factors. Dose intervals should not exceed one week when rebuilding dose.

The previous extract has expired or is near expiry: The dating period for allergenic extracts indicates the time that they can be expected to remain potent under ideal storage conditions (2 to 8°C) [see How Supplied/Storage and Handling (16)]. Some loss of potency occurs even when stored under ideal conditions, therefore extracts should not be stored beyond the expiration date. Instead, a new lot of should be used (see "Changing to a different lot of extract", above)

Changing from non-stabilized to human serum albumin (HSA) stabilized diluents: Allergenic extracts diluted with HSA and 0.4% phenol are more potent than extracts diluted with diluents that do not contain stabilizers. When switching from a non-stabilized to an HSA stabilized diluent, consider lowering the dose for immunotherapy.

2.2.2 Administration of Immunotherapy

Administer immunotherapy by subcutaneous injection in the lateral aspect of the arm or thigh. Avoid injection directly into any blood vessel.

- The optimal interval between doses of allergenic extract varies among individuals. Injections are usually given 1 or 2 times per week until the maintenance dose is reached, at which time the injection interval is increased to 2, 3, and finally 4 weeks.
- Because most adverse reactions occur within 30 minutes after injection, patients should be kept under observation for at least 30 minutes.^2 For high risk patients 30 minutes of observation may not be sufficient.

2.3 Dilution Preparation

To prepare dilutions for intradermal testing and immunotherapy, start with a 5,000, 10,000, or 30,000 Allergy Units/mL stock concetrate, and prepare a 1:10 dilution by adding 0.5 mL of concentrate to 4.5 mL of sterile aqueous diluent. Subsequent dilutions are made in a similar manner (see Table 2).

Table 2. Ten-fold Dilution Series for Intradermal Testing and Immunotherapy
Dilution | Extract | Diluent | AU/mL* | AU/mL | AU/mL
0 | Concentrate |  | 5,000 | 10,000 | 30,000
1 | 0.5 mL Concentrate | 4.5 mL | 500 | 1,000 | 3,000
2 | 0.5 mL Dilution 1 | 4.5 mL | 50 | 100 | 300
3 | 0.5 mL Dilution 2 | 4.5 mL | 5 | 10 | 30
4 | 0.5 mL Dilution 3 | 4.5 mL | 0.5 | 1 | 3
5 | 0.5 mL Dilution 4 | 4.5 mL | 0.05 | 0.1 | 0.3
6 | 0.5 mL Dilution 5 | 4.5 mL | 0.005 | 0.01 | 0.03

* Allergy Units

3 DOSAGE FORMS AND STRENGTHS

For immunotherapy, concentrated extracts are diluted in normal saline, buffered saline, albumin saline or 10% glycerosaline. For intradermal testing extracts may be diluted in normal saline, buffered saline, or albumin saline.

Greer Standardized Mite Extract D. farinae and Greer Standardized Mite Extract D. pteronyssinus are supplied as stock concentrates containing 10,000 Allergy Units/mL and Greer Standardized Mite Extract mixture (D. farinae and D. pteronyssinus) is supplied as a stock mixture concentrate containing 5,000 Allergy Units/mL of each species for use in percutaneous skin testing.

Greer Standardized Mite Extract D. farinae and Greer Standardized Mite Extract D. pteronyssinus are supplied as stock concentrates containing 5,000, 10,000, or 30,000 Allergy Units/mL. Greer Standardized Mite Extract mixture (D. farinae and D. pteronyssinus) is supplied as a stock mixture concentrate containing 5,000 and 15,000 Allergy Units/mL of each species for use in intradermal testing and immunotherapy.

4 CONTRAINDICATIONS

None.

5 WARNINGS AND PRECAUTIONS

5.1 Serious Systemic Reactions

All concentrates of Greer Standardized Mite Extracts have the ability during skin testing and immunotherapy to elicit serious systemic reactions including anaphylactic shock and death [see Adverse Reactions (6)].

A review of the literature indicates that the incidence of near-fatal reactions to immunotherapy, defined as severe respiratory compromise, hypotension, or both, and requiring emergency treatment with epinephrine, has been estimated as 5.4 events per million injections in a 10-year retrospective survey of allergists.^3 Fatalities from immunotherapy injections have been estimated to occur at a rate of approximately one death per 2.0 to 2.8 million injections in 4-, 10- and 12-year retrospective surveys of allergists.^4-6

Because of the danger of serious reactions, caution is required in testing and treating high risk patients and those with medical conditions that reduce their ability to survive a serious systemic adverse event.

High-risk patients are defined as those patients:

- with labile or steroid-dependent asthma, particularly in those suffering an exacerbation of their symptoms at the time of extract administration;
- with extreme sensitivity to a particular allergen(s);
- who are currently using beta blockers;
- who are receiving an accelerated immunotherapy build-up schedule (e.g., rush immunotherapy);
- who are being changed from one allergenic extract to another;
- who are receiving high doses of allergenic extracts.

High risk patients have had fatal reactions. In addition, patients not high-risk but on beta blockers have had fatal reactions because beta blockers interfere with beta adrenergics such as epinephrine used in treatment or anaphylaxis.

Patients should be kept under observation for a minimum of 30 minutes after receiving allergenic extracts so that any adverse reaction can be observed and properly handled.^2

Medications to treat systemic reactions, as well as emergency equipment should be available for immediate use. Extracts must only be administered by persons who are aware of the risk of systemic reactions, including anaphylaxis; are capable of handling such reactions; and have the necessary drugs and equipment on hand to do so.

5.2 Patients on Beta Blockers

Patients receiving beta blockers may be unresponsive to the usual doses of epinephrine used to treat serious systemic reactions, including anaphylaxis. Inhalant allergy immunotherapy should be approached with caution in patients taking beta blockers. The risks of anaphylaxis in these patients should be carefully weighed against the benefits of immunotherapy [see Drug Interactions (7.1)].

5.3 Autoimmune Disease

Immunotherapy should be given cautiously to patients with other immunologic diseases and only if the risk from exposure to the allergen is greater than the risk of exacerbating the underlying disorder.^2

6 ADVERSE REACTIONS

Systemic reactions consist primarily of allergic symptoms, such as generalized skin erythema, urticaria, pruritus, angioedema, rhinitis, wheezing, laryngeal edema, and hypotension. Additional symptoms that are not usually associated with allergy also may occur, such as nausea, emesis, abdominal cramps, and diarrhea. Serious reactions may cause shock, loss of consciousness, and even death. Based on published studies,^7,8 systemic reactions occur in less than 1% of patients receiving conventional immunotherapy to greater than 36% in some studies of patients receiving rush immunotherapy.

Local reactions at the injections site are the most commonly occurring reactions (e.g., erythema, itching, swelling, tenderness, pain). Although most adverse systemic reactions occur within 30 minutes of injection (some within minutes of extract exposure), such reactions also can occur up to six hours after skin tests or immunotherapy [see Dosage and Administration (2.2)].^9

7 DRUG INTERACTIONS

7.1 Beta Adrenergic Drugs

Patients receiving beta blocker drugs may not be responsive to beta adrenergic drugs used to treat anaphylaxis^10, and may wish to temporarily postpone treatment day of skin testing. All such decisions should be made in consultation with the physician [see Warnings and Precautions (5.2)].

7.2 Antihistamines^1

Skin testing with allergenic extracts should not be performed within 2-3 days of first-generation H1-histamine receptor blockers (e.g., clemastine, diphenhydramine) and within 3 to 10 days of second-generation antihistamines (e.g., loratadine, terfenadine), except for astemizole, which requires an interval of 30-60 days between allergenic extract exposure and use. These products suppress histamine skin test reactions and could mask a positive response.

7.3 Topical Corticosteroids and Topical Anesthetics^1

Topical corticosteroids may suppress skin reactivity and should be discontinued at the skin test site for at least 2-3 weeks before skin testing. Topical local anesthetics may suppress flare responses and should be avoided at skin test sites.

7.4 Tricyclic Antidepressants^1

Tricyclic antidepressants can have potent antihistamine effects and will affect skin testing. Since use of tricyclics may alter skin test results, dosing for both skin testing and immunotherapy should be done with caution. If tricyclic medication has been recently discontinued, allow 7-14 days prior to skin testing to obviate the antihistamine effect. The risk of anaphylaxis in these patients should be carefully weighed against the risks and benefits of stopping tricyclics.

7.5 Other Drugs

The suppressive action of other drugs should be considered and emphasizes the need for a histamine positive-control test.

8 USE IN SPECIFIC POPULATIONS

8.1 Pregnancy

Pregnancy Category C: Animal reproduction studies have not been conducted with Greer Standardized Mite Extracts. It is also not known whether Greer Standardized Mite Extracts can cause fetal harm when administered to a pregnant woman or whether they can affect reproduction capacity. Standardized Mite Extracts should be given to a pregnant woman only if clearly needed.

Studies have not been performed in animals to determine whether extracts affect fertility in males or females, have teratogenic potential, or have other adverse affects on the fetus. Exercise caution in testing or treating pregnant females because a systemic reaction may cause maternal cardiovascular compromise leading to fetal distress with sequelae.

8.3 Nursing Mothers

It is not known whether allergenic extracts or their antigens are excreted in human milk. Because many drugs are excreted in human milk, exercise caution when extracts are administered to a nursing woman.

8.4 Pediatric Use

No studies have systematically examined differences in response to immunotherapy among child and adult patients. Children appear to tolerate injections of allergenic extracts very well.^2 Very young children (under age 5) can have difficulty cooperating with an immunotherapy program and for this reason, the physician should consider the benefits and risks of immunotherapy and indiviualize treatment in patients under the age of 5 years [see Warnings and Precautions (5)].

8.5 Geriatric Use

Clinical studies of Greer Standardized Mite Extract did not include sufficent numbers of subjects aged 65 and older to determine whether they respond differently from younger subjects. Other reported clinical experiences has not identified differences in responses between the elderly and younger patients. In general, dose selection for an elderly patient should be cautious, usually starting at the low end of the dosing range, reflecting the greater frequency of concomitant disease or other drug therapy including beta blockers.^2

10 OVERDOSAGE

For all allergenic extracts the therapeutic dose varies per indiviual. If a dose exceeds the window for a particular patient this may be considered an overdose and the patient may experience anaphylaxis. Systemic reactions are uncommon after injection, but if the patient receives more extract than can be tolerated at that particular time, and begins to experience immediate hypersensitivity anaphylaxis, institute emergency treatment by trained personnel.

Overdosage may occur because of an error in the volume of extract or incorrect diluents injected. An overdose may also occur when, in addition to immunotherapy, the patient is exposed concomitantly to similar environmental allergens. In the event of a systemic reaction, the preparation of allergen and dosage schedule should be carefully reviewed.

11 DESCRIPTION

Greer Standardized Mite (Dermatophagoides farinae and/or Dermatophagoides pteronyssinus) extracts are sterile solutions used for intradermal testing or subcutaneous immunotherapy. Each vial contains 5,000, 10,0000 or 30,000 Allergy Units/mL of sterile mite extract (D. farinae and/or D. pteronyssinus), 50% glycerin v/v, and 0.4% phenol (preservative). Inert ingredients include 0.50% sodium chloride for isotonicity and 0.25% sodium bicarbonate as a buffer.

For immunotherapy, concentrated extracts are diluted in normal saline, buffered saline, albumin saline or 10% glycerosaline based on patient's reactivity. For intradermal testing, extracts may be diluted in normal saline, buffered saline, or albumin saline.

Source materials for the extract are whole mite bodies. The mites are cultured, handled, and cleaned to remove at least 99% of the food medium. The medium containes no material of human origin.

The mite extract is standardized by comparison to a reference preparation supplied by the Center for Biologics Evaluation and Research of the FDA, labeled 10,000 Allergy Units/mL. The relative potency of the extract is determined by ELISA inhibition compared to the FDA mite reference, and is labeled in Allergy Units/mL.

12 CLINICAL PHARMACOLOGY

Dust mites belonging to the genus Dermatophagoides are indoor allergens found in humid geographic locations worldwide. D. farinae and D. pteronyssinus occur widely with most homes in the United States coinhabited by both species.^11

12.1 Mechanism of Action

The complete mechanisms of allergen immunotherapy are not clear and remain the subject of investigation. The allergic reaction is dependent on the presence of allergen-specific immunoglobulin E (IgE) antibodies that are bound to specific receptors on mast cells and basophils. The presence of IgE antibodies sensitizes these cells, and upon interaction with the appropriate allergens, histamine and other mediators are released which produce local or systemic responses in sensitive individuals, and characteristic symptoms of atopic diseases, such as allergic rhinitis and allergic asthma. Changes in serum antibody and T-lymphocyte responses resulting from immunotherapy have been demonstrated, and these changes often correlate closely with clinical (symptom) improvements. Specific mechanisms may vary depending on the nature of the allergic disease, the allergenic specificities of patients and populations, extract formulations, route of administration, dose and duration of treatment.^2

Subcutaneous administration of allergenic extracts is known to elicit numerous immunological changes that are both time and dose-dependent. Many of these changes appear to be related to (or a precursor to) improvements in symptoms and other clinical parameters, as noted above. Specific changes found after immunotherapy with dust mite extracts include significant increases in mite-specific IgG4 antibodies^12, interleukin-10-positive T cells, and several T-cell receptors, and significant decreases in serum nitric oxide, eosinophil catonic protein, interleukin-4-positive T cells and IgE-mediated basophil histamine release.^13

13 NONCLINICAL TOXICOLOGY

13.1 Carcinogenesis, Mutagenesis or Impairment of Fertility

No studies in animals have been performed to evaluate carcinogenecity, mutagenicity or impairment of fertility.

14 CLINICAL STUDIES

The dust mites D. farinae and D. pteronyssinus are the major source of allergens in house dust.^14 The efficacy of immunotherapy for Type I hypersensitivity (i.e. allergy) to airborne allergens^2,15,16 including dust mite has been well established. Specifically, immunotherapy for allergic hypersensitivity to house dust mite allergens has been addressed in a 1995 Cochrane meta-analysis of 20 randomized, controlled trials of immunotherapy,^17 and two subsequent updated Cochrane meta-analysis published in 1999^18 and 2003^19. In addition, efficacy for immunotherapy in rush or cluster protocols, in which the dose escalation is compressed over days or weeks, has also been demonstrated.^20,21

15 REFERENCES

1. Bernstein IL, Li JT, Bernstein Dl, et al. Allergy dignostic testing: and updated practice parameter. Ann Allergy Asthma Immunol 2008;100:S1-148.
2. Bernstein IL, Li JT, Bernstein Dl, et al. Allergy dignostic testing: and updated practice parameter. Ann Allergy Asthma Immunol 2008;100:S1-148.
3. Amin HS, Liss GM, Bernstein Dl. Evaluation of near-fatal reactions to allergen immunotherapy injections. J Allergy Clin Immunol 2006;117:169-75.
4. Lockey RF, Benedict LM, Turkeltaub PC, Bukantz SC. Fatalities from immunotherapy (IT) and skin testing (ST). J Allergy Clin Immunol 1987;79:660-77.
5. Reid MJ, Lockey RF, Turkeltaub PC, Platts-Mills TA. Survey of fatalities from skin testing and immunotherapy 1985-1989. J Allergy Clin Immunol 1993;92:6-15.
6. Bernstein DI, Wanner M, Borish L, Liss GM. Twelve-year survey of fatal reactions to allergen injections and skin testing: 1990-2001. J Allergy Clin Immunol 2004;113:1129-36.
7. Lockey RF, Nicoara-Kasti GL, Theodoropoulos DS, Bukantz SC. Systemic reactions and fatalities associated with allergen immunotherapy. Ann Allergy Asthma Immunol 2001;87(suppl 1):47-55.
8. Malling HJ. Minimising the risks of allergen-specific injection immunothreapy. Drug Saf 2000;23:323-332.
9. Greenberg MA, Kaufman CR, Gonzalez GE, et. al. Late and immediate systemic-allergic reactions to inhalant allergen immunotherapy. J Allergy Clin Immunol 1986;77:865-870.
10. Jacobs RL, Rake GW, Jr., Fournier DC, Chilton RJ, Culver WG, Beckmann CH. Potentiated anaphylaxis in patients with drug-induced beta-adrenergic blockade. J Allergy Clin Immunol 1981;68:125-7.
11. Arlian L, Bernstein D, Bernstein L, et al. Prevalence of dust mites in the homes of people with asthma living in eight different geopgraphic areas of the United States. J Allergy Clin Immunol 1992;90:292-300.
12. Chapman MD, Platts-Mills TA, Gabriel M, et al. Antibody response following prolonged hyposensitization with Dermatophagoides pteronyssinus extract. Arch Allergy Appl Immunol 1980;61:431-40.
13. Gurka G, Rocklin R. Immunologic responses during allergen-specific immunotherapy for respiratory allergy. Ann Allergy 1988;61:239-45.
14. Voorhorst R, Spieksma FTM, Varekamp H. House Dust Atopy and the House Dust Mite. Leiden: Stafleu's Scientific Publishing Co; 1969.
15. Maunsell K, Wraith DG, Hughes AM. Hyposensitisation in mite asthma. Lancet 1971;1:967-8.
16. Mite Allergy Subcommittee of the Research Committee of the British Thoracic Association. A trial of house dust mite extract in bronchial asthma. Br J Dis Chest 1979;73:260-70.
17. Abramson MJ, Puy RM, Weiner JM. Is allergen immunotherapy effective in asthma? A meta-analysis of randomized controlled trials. Am J Respir Crit Care Med 1995; 151:969-74.
18. Abramson M, Puy R, Weiner J. Immunotherapy in asthma: an updated systematic review. Allergy 1999;54:1022-41.
19. Abramson MJ, Puy RM, Weiner JM. Allergen immunotherapy for asthma. The Cochrane Database of Systematic Reviews 2003;CD001186.
20. Bousquet J, Calvayrac P, Guerin B, et al. Immunotherapy with a standardized Dermatophagoides pteronyssinus extract. I. In vivo and in vitro parameters after a short course of treatment. J Allergy Clin Immunol 1985;76:734-44.
21. Garcia-Ortega P, Merelo A, Marrugat J, Richart C. Decrease of skin and bronchial sensitization following short-intensive scheduled immunotherapy in mite-allergic asthma. Chest 1993;103:183-7.

16 HOW SUPPLIED/STORAGE AND HANDLING

16.1 How Supplied

Mite extracts in 50% Glycero-Coca solution are supplied as follows:

D. farinae: NDC 22840-0033 | 5,000 Allergy Units/mL, 10, 30, and 50 mL vials
D. farinae: NDC 22840-0034 | 10,000 Allergy Units/mL, 5 mL percutaneous test vial
D. farinae: NDC 22840-0034 | 10,000 Allergy Units/mL, 10, 30, and 50 mL vials
D. pteronyssinus: NDC 22840-0035 | 5,000 Allergy Units/mL, 10, 30, and 50 mL vials
D. pteronyssinus: NDC 22840-0036 | 10,000 Allergy Units/mL, 5 mL percutaneous test vial
D. pteronyssinus: NDC 22840-0036 | 10,000 Allergy Units/mL, 10, 30, and 50 mL vials
D. farinae/ D. pteronyssinus mixture: NDC 22840-0037 | 5,000 Allergy Units/mL each species, 5 mL percutaneous test vial
D. farinae/ D. pteronyssinus mixture: NDC 22840-0037 | 5,000 Allergy Units/mL each species, 10, 30, and 50 mL vials
D. farinae: NDC 22840-0038 | 30,000 Allergy Units/mL, 10, 30, and 50 mL vials
D. pteronyssinus: NDC 22840-0039 | 30,000 Allergy Units/mL, 10, 30, and 50 mL vials
D. farinae/ D. pteronyssinus mixture: NDC 22840-0040 | 15,000 Allergy Units/mL each species, 10, 30, and 50 mL vials

16.2 Storage and Handling

Store dust mite extract at 2 to 8°C (36 to 46°F).

Keep dust mite extract at 2 to 8°C (36 to 46°F) during office use.

Dilutions of concentrated extract result in a glycerin content of less than 50% which results in reduced stability of the extracts. 1:100 dilutions should be kept no longer than a month, and more dilute solutions no more than a week. The potency of a dilution can be checked by skin test comparison to a fresh dilution of the extract on a known mite allergic individual.

17 PATIENT COUNSELING INFORMATION

Instruct the patient to remain in the office for observation for a minumum of 30 minutes after an injection; longer, if deemed necessary for the individual.

Caution patients that reactions may occur more than 30 minutes after skin testing or an injection.

Instruct patient to recognize the following symptoms as adverse reactions and to immediately return to the office or immediately seek other medical attention if any of these symptoms occur following an injection.

- Unusual swelling and/or tenderness at the injection site
- Swelling of face and/or mouth
- Sneezing, coughing or wheezing
- Shortness of breath
- Nausea
- Dizziness or faintness

Manufacturer:

U.S. License No. 308

Greer Laboratories, Inc.

Lenoir, NC 28645 U.S.A